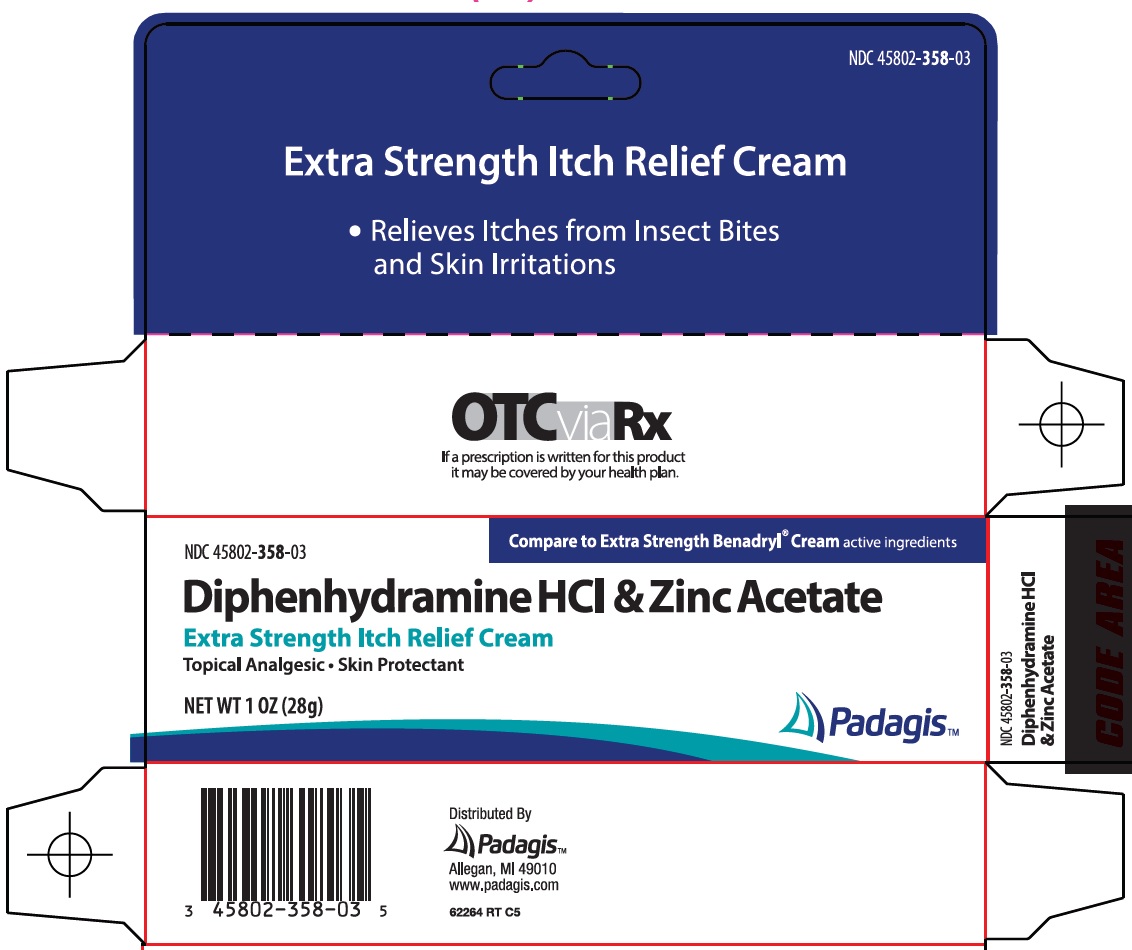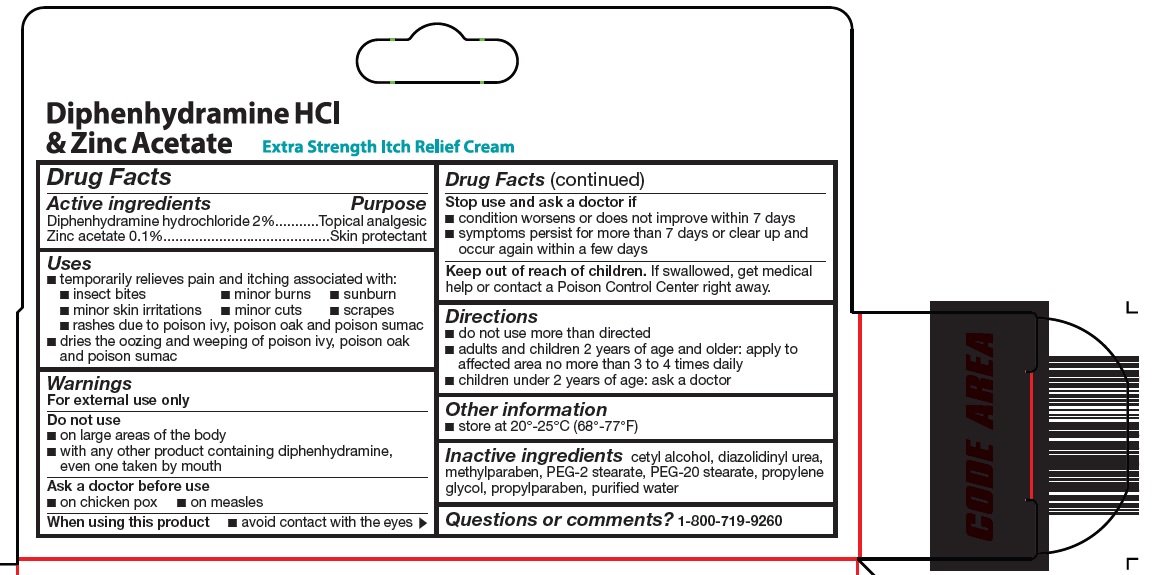 DRUG LABEL: diphenhydramine hcl and zinc acetate
NDC: 45802-358 | Form: CREAM
Manufacturer: Padagis Israel Pharmaceuticals Ltd
Category: otc | Type: HUMAN OTC DRUG LABEL
Date: 20260114

ACTIVE INGREDIENTS: DIPHENHYDRAMINE HYDROCHLORIDE 2 g/100 g; ZINC ACETATE 0.1 g/100 g
INACTIVE INGREDIENTS: CETYL ALCOHOL; DIAZOLIDINYL UREA; METHYLPARABEN; PROPYLENE GLYCOL; PROPYLPARABEN; WATER; PEG-20 STEARATE; DIETHYLENE GLYCOL MONO- AND DIPALMITOSTEARATE

Diphenhydramine HCl & Zinc Acetate Drug Facts

Active ingredients

Diphenhydramine hydrochloride 2%

Zinc acetate 0.1%

Purpose

Topical analgesic

Skin protectant

Uses

- temporarily relieves pain and itching associated with:
  - insect bites
  - minor burns
  - sunburn
  - minor skin irritations
  - minor cuts
  - scrapes
  - rashes due to poison ivy, poison oak and poison sumac
- dries the oozing and weeping of poison ivy, poison oak and poison sumac

Warnings

For external use only

Do not use

- on large areas of the body
- with any other product containing diphenhydramine, even one taken by mouth

Ask a doctor before use

- on chicken pox
- on measles

When using this product

- avoid contact with the eyes

Stop use and ask a doctor if

- condition worsens or does not improve within 7 days
- symptoms persist for more than 7 days or clear up and occur again within a few days

Keep out of reach of children.

If swallowed, get medical help or contact a Poison Control Center right away.

Directions

- do not use more than directed
- adults and children 2 years of age and older: apply to affected area no more than 3 to 4 times daily
- children under 2 years of age: ask a doctor

Other information

- store at 20°-25°C (68°-77°F)

Inactive ingredients

cetyl alcohol, diazolidinyl urea, methylparaben, PEG-2 stearate, PEG-20 stearate, propylene glycol, propylparaben, purified water

Questions or comments?

1-800-719-9260

Principal Display Panel

Extra Strength Itch Relief Cream

• Relieves Itches from Insect Bites and Skin Irritations

Compare to Extra Strength Benadryl® Cream active ingredients

Diphenhydramine HCl & Zinc Acetate

Extra Strength Itch Relief Cream

Topical Analgesic • Skin Protectant

NET WT 1 OZ (28 g)

Padagis™